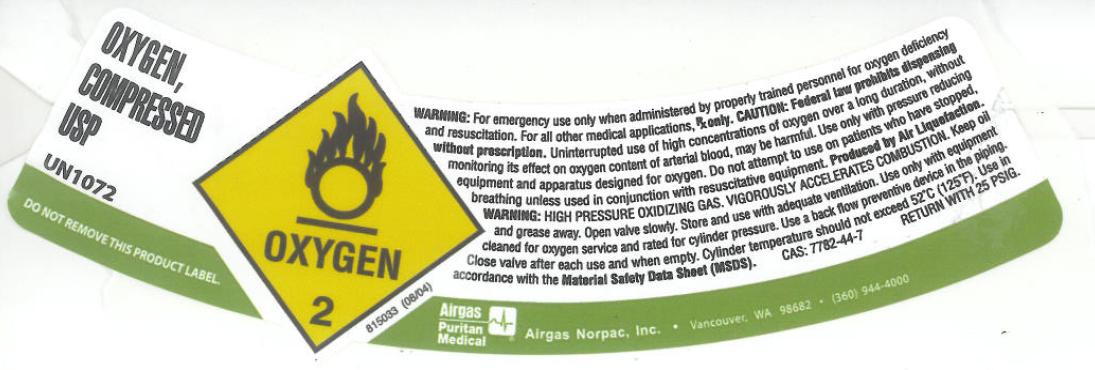 DRUG LABEL: Oxygen
NDC: 57472-001 | Form: GAS
Manufacturer: AIRGAS NOR PAC INC
Category: prescription | Type: HUMAN PRESCRIPTION DRUG LABEL
Date: 20110505

ACTIVE INGREDIENTS: Oxygen 995 mL/1 L

oxygen

PACKAGE LABEL

OXYGEN, Compressed USP UN1072 DO NOT REMOVE THIS PRODUCT LABEL.
OXYGEN 2 815033 (08/04)
WARNING: For emergency use only when administered by properly trained personnel for oxygen deficiency and resuscitation. For all other medical applications, Rx ONLY. CAUTION: Federal law prohibits dispensing without prescription. Uninterrupted use of high concentrations of oxygen over a long duration, without monitoring its effect on oxygen content of arterial blood, may be harmful. Use only with pressure reducing equipment and apparatus designed for use with oxygen. Do not attempt to use on patients who have stopped breathing unless used in conjunction with resuscitative equipment. Produced by Air Liquefaction. WARNING: HIGH PRESSURE OXIDIZING GAS. VIGOROUSLY ACCELERATES COMBUSTION. Keep oil and grease away. Open valve slowly. Store and use with adequate ventilation. Use only with equipment cleaned for oxygen service and rated for cylinder pressure. Use a back flow preventive device in the piping. Close valve after each use and when empty. Cylinder temperature should not exceed 52 C (125F). Use in accordance with Material Safety Data Sheet (MSDS).
CAS: 7782-44-7 RETURN WITH 25 PSIG
Airgas Puritan Medical Airgas Norpac, Inc. Vancouver, WA 98682 (360) 944 4000